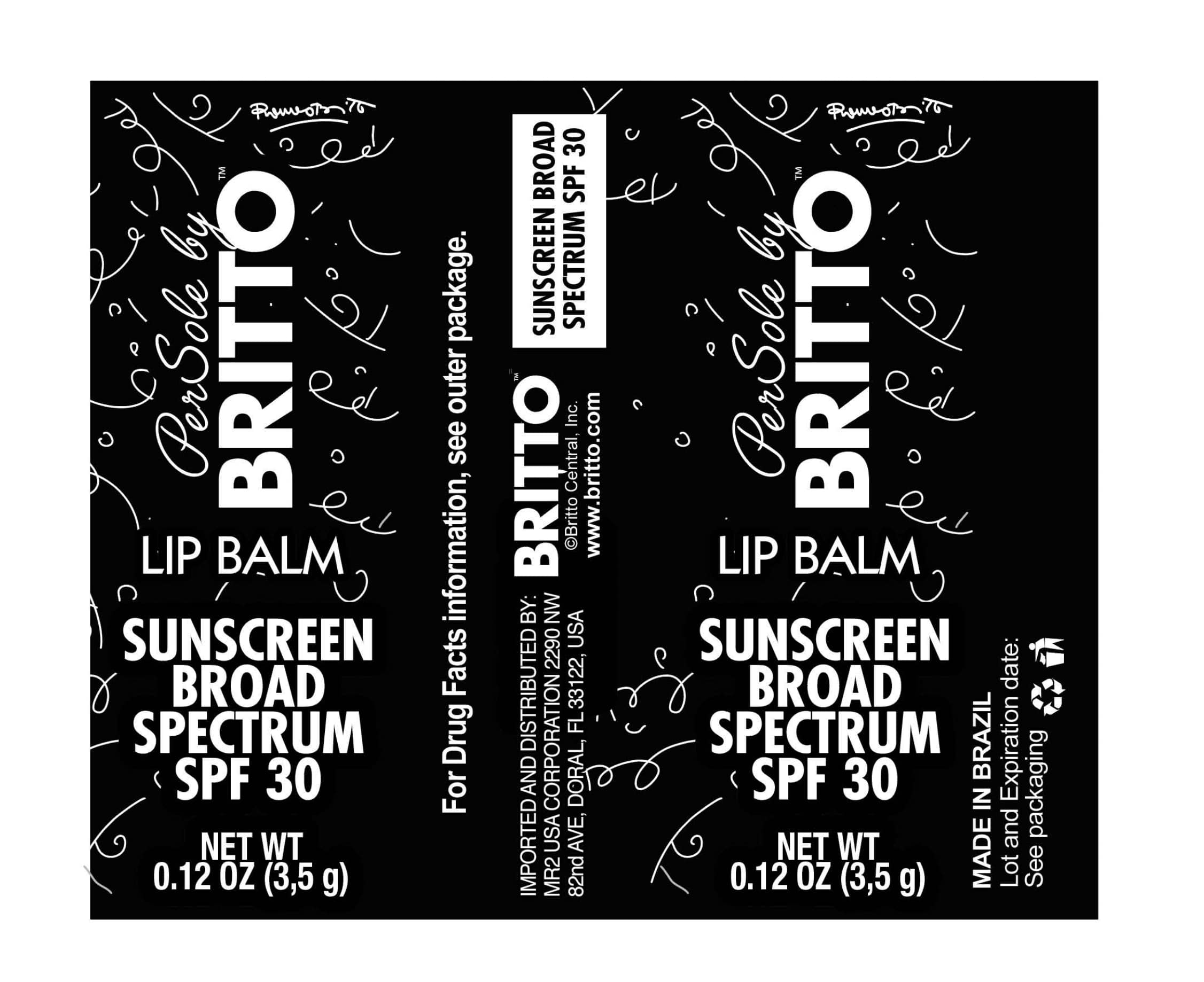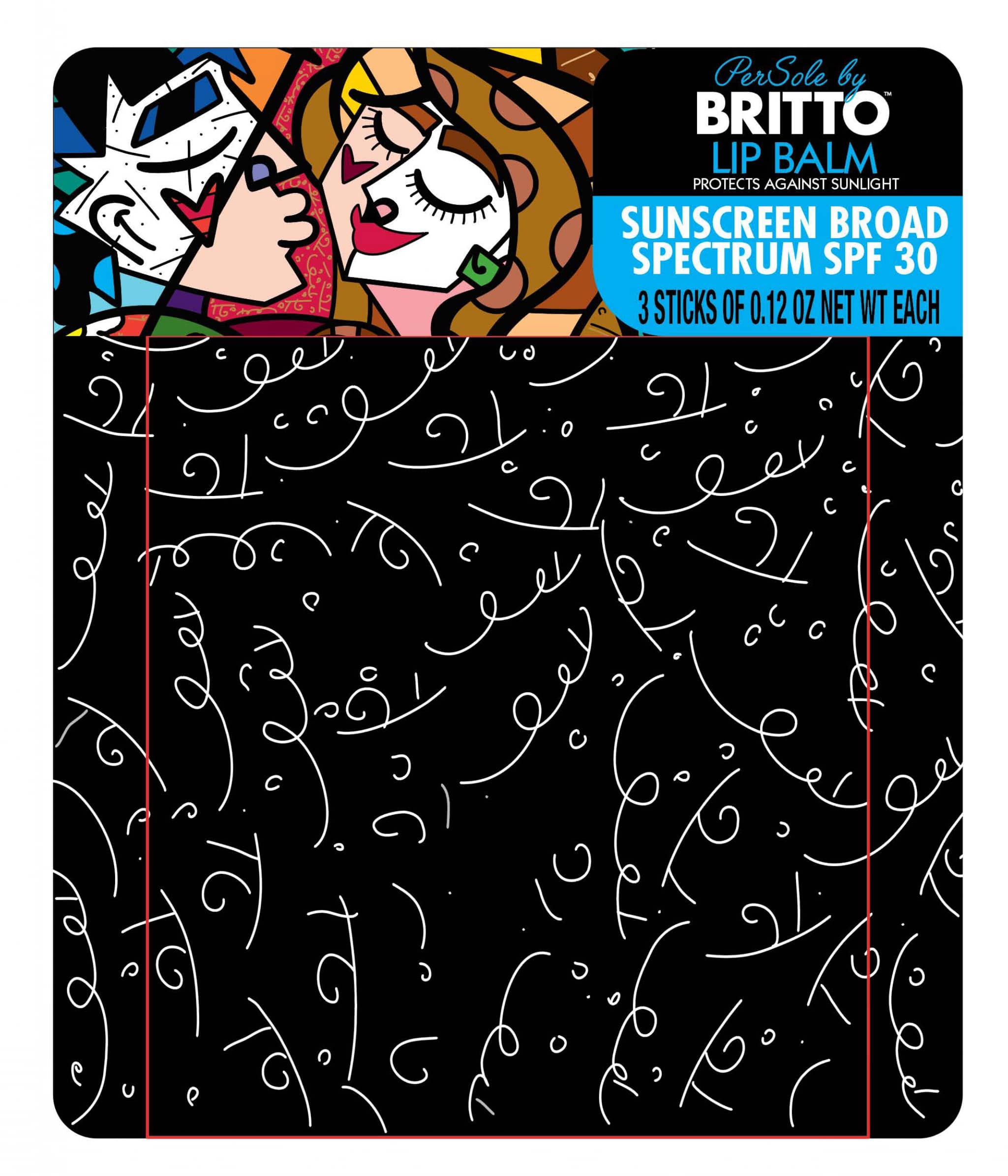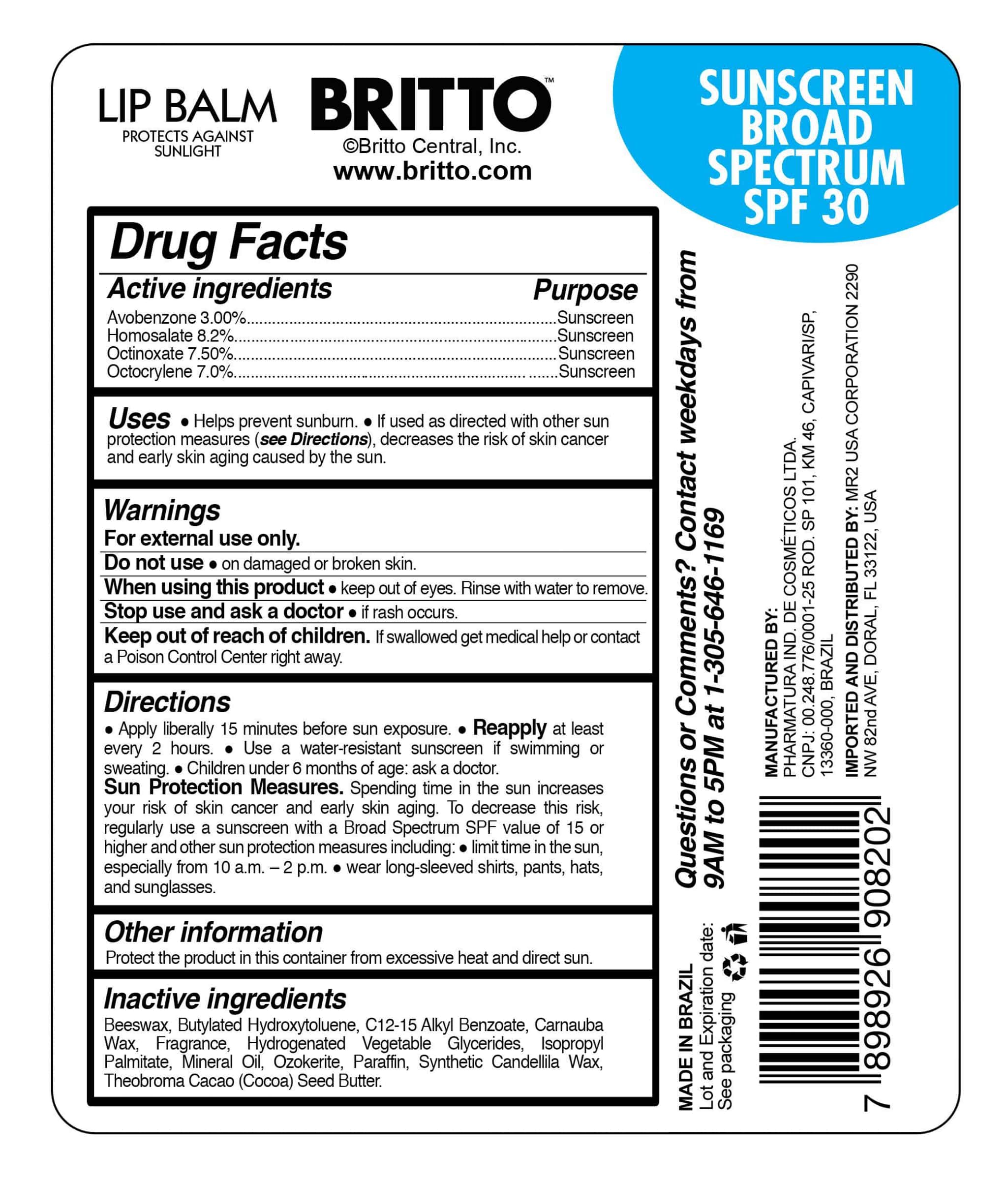 DRUG LABEL: Per Sole by Britto Lip Balm Sunscreen Broad Spectrum SPF 30
NDC: 77069-001 | Form: LIPSTICK
Manufacturer: MR2 USA Corporation
Category: otc | Type: HUMAN OTC DRUG LABEL
Date: 20201227

ACTIVE INGREDIENTS: OCTINOXATE 7.5 g/100 g; AVOBENZONE 3 g/100 g; HOMOSALATE 8.2 g/100 g; OCTOCRYLENE 7 g/100 g
INACTIVE INGREDIENTS: ISOPROPYL PALMITATE 3 g/100 g; COCOA BUTTER 8 g/100 g; CERESIN 2.8 g/100 g; BUTYLATED HYDROXYTOLUENE 0.05 g/100 g; ALKYL (C12-15) BENZOATE 10 g/100 g; MINERAL OIL 7 g/100 g; WHITE WAX 3 g/100 g; CARNAUBA WAX 6 g/100 g; PARAFFIN 6.2 g/100 g

NO CHANGE NOTIFICATION

Principal Display Panel - Statement of identity

Lip Balm Sunscreen Broad Spectrum SPF 30

Drug Facts Panel - Active Ingredients

Avobenzone 3.0% ----- Sunscreen

Homosalate 8.2% ----- Sunscreen

Octinoxate 7.5% ------- Sunscreen

Octocrylene 7.0% ----- Sunscreen

Drug Facts Panel - Purpose

Purpose: sunscreen

Drug Facts Panel - Use

Helps prevent sunburn.

If used as directed with other sun protection measures (see Directions), decreases the risk of skin cancer and early skin ageing caused by the sun.

Drug Facts Panel - Warnings

For external use only.

Do not use on damaged or broken skin.

When using this product keep out of eyes. Rinse with water to remove.

Stop use and ask a doctor if rash occurs.

Keep out of reach of children. If swallowed get medical help or contact a Poison Control Center right away.

Drug Facts Panel - Warnings - Do not use

Do not use on damaged or broken skin.

Drug Facts Panel - Warnings - When using this product

When using this product keep out of eyes. Rinse with water to remove.

Drug Facts Panel - Warnings - Stop use

Stop use and ask a doctor if rash occurs.

Drug Facts Panel - Warnings - Keep out of reach of children,

Keep out of reach of children. If swallowed get medical help or contact a Poison Control Center right away.

Drug Facts Panel - Directions

Apply liberally 15 minutes before sun exposure.

Reapply at least every 2 hours.

Use a water-resistant sunscreen if swimming or sweating.

Children under 6 months of age: ask a doctor.

Sun Protection Measures. Spending time in the sun increases your risk of skin cancer and early skin aging. To decrease this risk, regularly use a sunscreen with a Broad Spectrum SPF value of 15 or higher and other sun protection measures including:  limit time in the sun, especially from 10 a.m.-2 p.m.  wear long-sleeved shirts, pants, hats, and sunglasses.

Drug Facts Panel - Other information

Protect the product in this container from excessive heat and direct sun.

Drug Facts Panel - Inactive ingredients

Beeswax, Butylated Hydroxytoluene, C12-15 Alkyl Benzoate, Carnauba Wax, Fragrance, Hydrogenated Vegetable Glycerides, Isopropyl Palmitate, Mineral Oil, Ozokerite, Paraffin, Synthetic Candellila Wax, Theobroma Cacao (Cocoa) Seed Butter.

Questions or comments

Contact weekdays from 9AM to 5PM at 1-305-646-1169.

Package Label - Principal Display Panel

NDC 77069-001-01

Level 1 - cylinder (stick)

NDC 77069-001-01

Level 2 - blister (3 x stick)